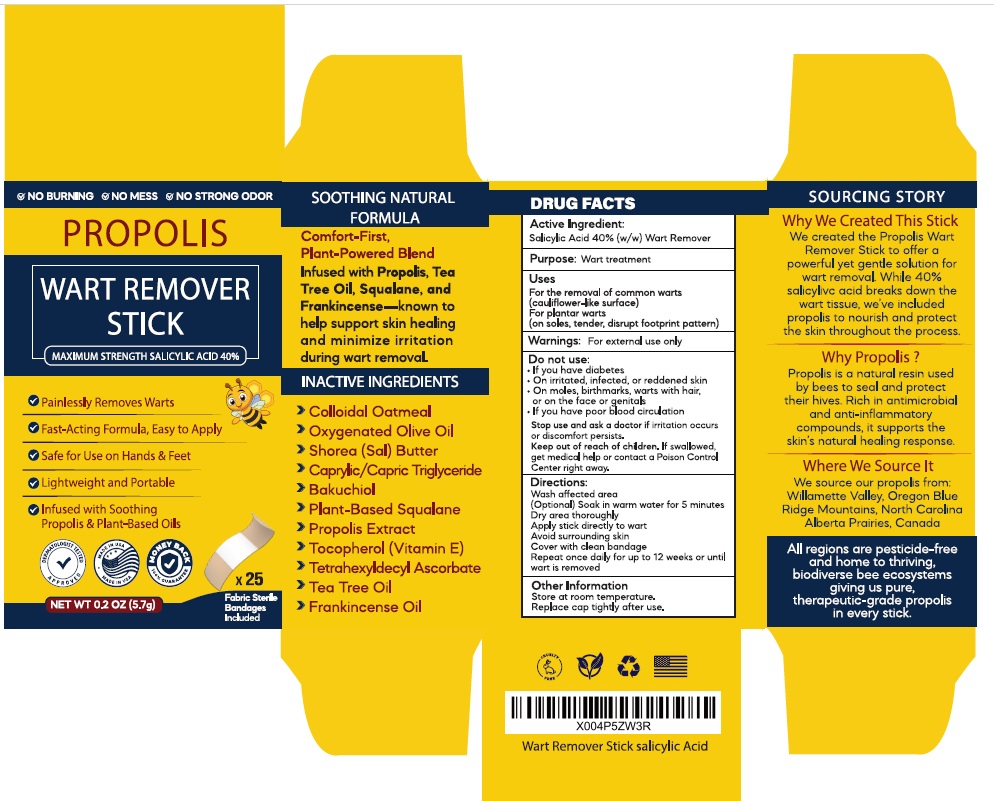 DRUG LABEL: Propolis Wart Remover Stick
NDC: 83004-029 | Form: STICK
Manufacturer: Rida LLC
Category: otc | Type: HUMAN OTC DRUG LABEL
Date: 20250825

ACTIVE INGREDIENTS: SALICYLIC ACID 40 g/100 g
INACTIVE INGREDIENTS: OATMEAL; OLIVE OIL; SHOREA STENOPTERA SEED BUTTER; TRICAPRIN; BAKUCHIOL; SQUALANE; PROPOLIS WAX; TOCOPHEROL; TETRAHEXYLDECYL ASCORBATE; TEA TREE OIL; FRANKINCENSE OIL

Active Ingredient

Salicylic acid 40% (w/w)

Purpose

Wart remover

Uses

For the removal of common warts (hands) and plantar warts (feet)

Warnings

- For external use only
- Do not use if you have diabetes
- On irritated, infected, or reddened skin
- On moles, birthmarks, warts with hair, or on the face or genitals
- If you have poor blood circulation

Stop use and ask a doctorif irritation occurs discomfort persists

Keep out of reach of children.If swallowed, get medical help or contact a Poison Control Center right away.

Do not use

- if you are a diabetic
- on irritated, infected, or reddened skin
- if you have poor blood circulation
- on warts with hair growing from them
- on moles or birthmarks
- on face, genitals, or mucous membranes

Stop use and ask a doctor if

irritation occurs or discomfort persists

Keep out of reach of children and pets.

If swallowed, get medical help or contact a Poison Control Center right away.

Directions

- Wash affected area
- Soak wart for 5 minutes in warm water
- Dry thoroughly
- Apply stick directly to wart
- Avoid surrounding skin
- Cover with a clean bandage
- Repeat once daily for up to 12 weeks or until wart is removed

Inactive Ingredients

Colloidal Oatmeal , Oxygenated Olive Oil , Shorea (Sal) Butter , Caprylic/Capric Triglyceride , Bakuchiol ,Squalane , Propolis Extract , Tocopherol (Vitamin E), Tetrahexyldecyl Ascorbate , Tea Tree Oil ,Frankincense Oil

Other Information

Store at room temperature. Replace cap tightly after use.